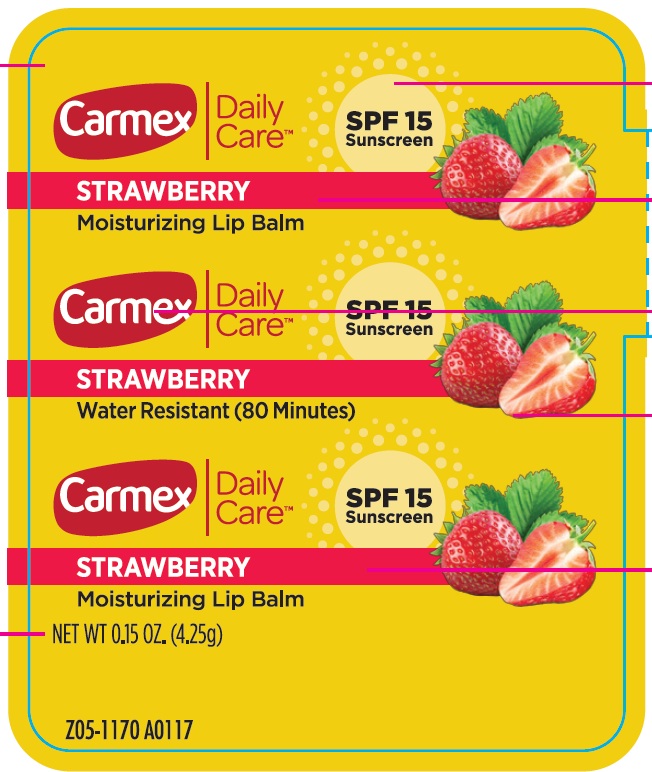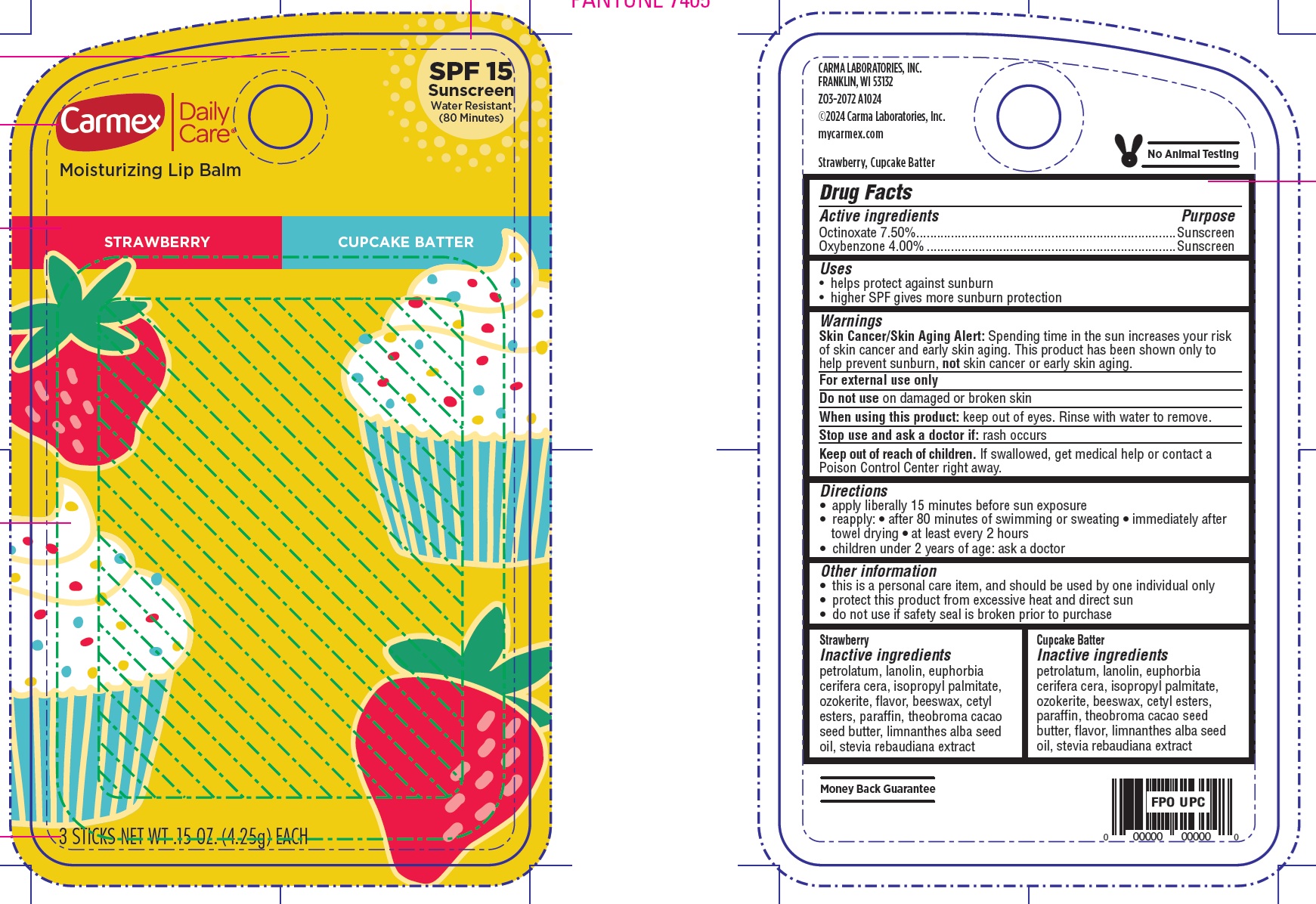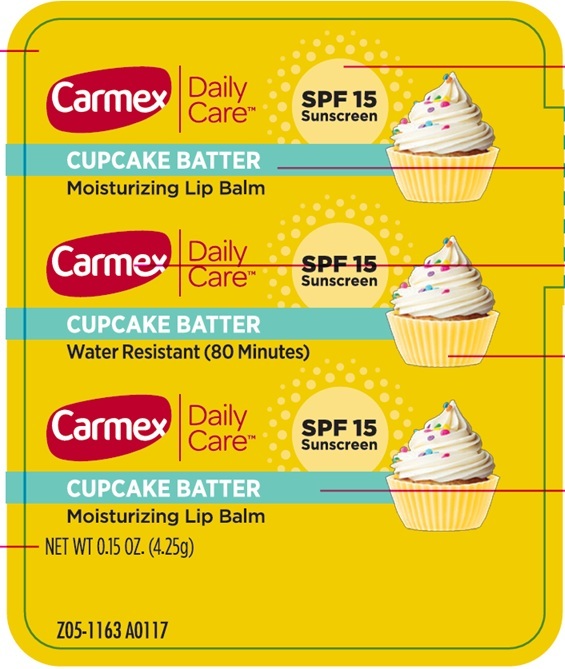 DRUG LABEL: Carmex Daily Care Moisturizing Lip Balm SPF 15
NDC: 10210-0091 | Form: KIT | Route: TOPICAL
Manufacturer: Carma Laboratories, Inc.
Category: otc | Type: HUMAN OTC DRUG LABEL
Date: 20250407

ACTIVE INGREDIENTS: OCTINOXATE 75 mg/1 g; OXYBENZONE 40 mg/1 g; OCTINOXATE 75 mg/1 g; OXYBENZONE 40 mg/1 g
INACTIVE INGREDIENTS: PETROLATUM; LANOLIN; ISOPROPYL PALMITATE; YELLOW WAX; CETYL ESTERS WAX; PARAFFIN; MEADOWFOAM SEED OIL; PETROLATUM; LANOLIN; ISOPROPYL PALMITATE; YELLOW WAX; CETYL ESTERS WAX; PARAFFIN; MEADOWFOAM SEED OIL

Carmex Daily Care Moisturizing Lip Balm SPF 15

Active ingredients

Octinoxate 7.50%

Oxybenzone 4.00%

Purpose

Sunscreen

Uses

- helps protect against sunburn
- higher SPF gives more sunburn protection

Warnings

Skin Cancer/Skin Aging Alert: Spending time in the sun increases your risk of skin cancer and early skin aging. This product has been shown only to help prevent sunburn, not skin cancer or early skin aging.

For external use only

Do not use

on damaged or broken skin

When using this product:

keep out of eyes. Rinse with water to remove.

Stop use and ask a doctor if:

rash occurs

Keep out of reach of children.

If swallowed, get medical help or contact a Poison Control Center right away.

Directions

• apply liberally 15 minutes before sun exposure

• reapply: • after 80 minutes of swimming or sweating • immediately after towel drying • at least every 2 hours

• children under 2 years of age: ask a doctor

Other information

• this is a personal care item, and should be used by one individual only

• protect this product from excessive heat and direct sun

• do not use if safety seal is broken prior to purchase

Strawberry Inactive ingredients

petrolatum, lanolin, euphorbia cerifera cera, isopropyl palmitate, ozokerite, flavor, beeswax, cetyl esters, paraffin, theobroma cacao seed butter, limnanthes alba seed oil, stevia rebaudiana extract

Cupcake Batter Inactive ingredients

petrolatum, lanolin, euphorbia cerifera cera, isopropyl palmitate, ozokerite, beeswax, cetyl esters, paraffin, theobroma cacao seed butter, flavor, limnanthes alba seed oil, stevia rebaudiana extract